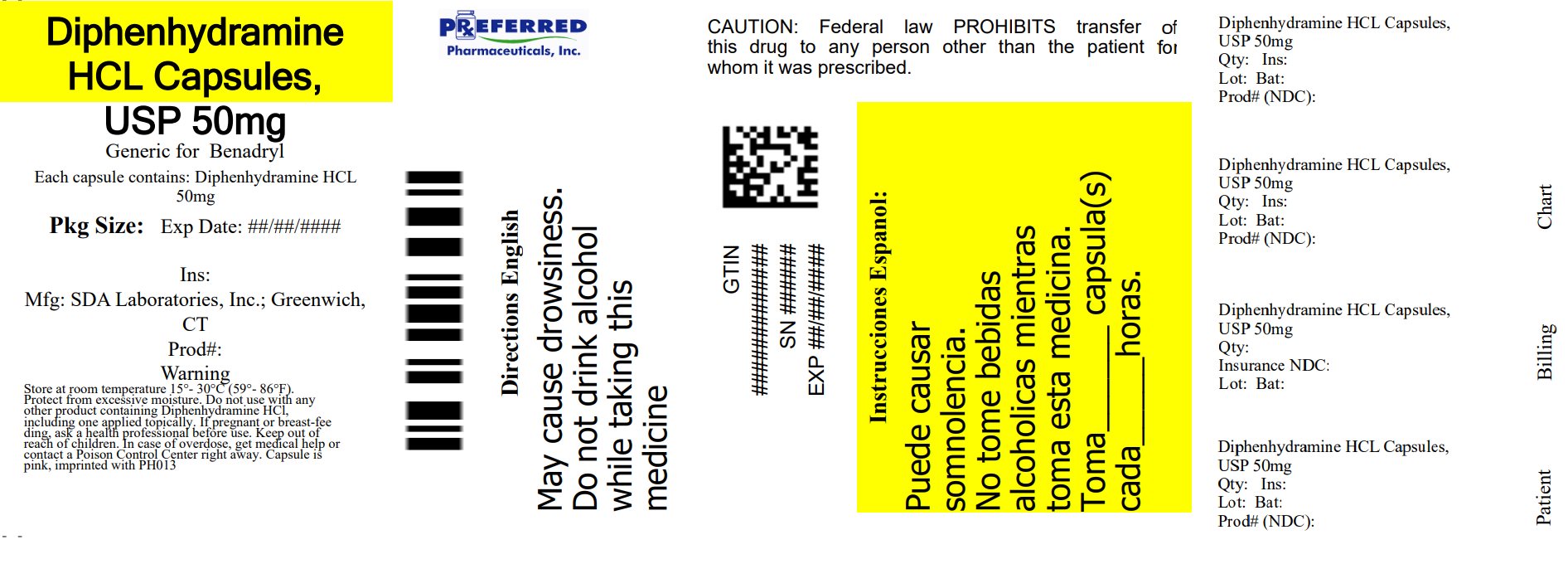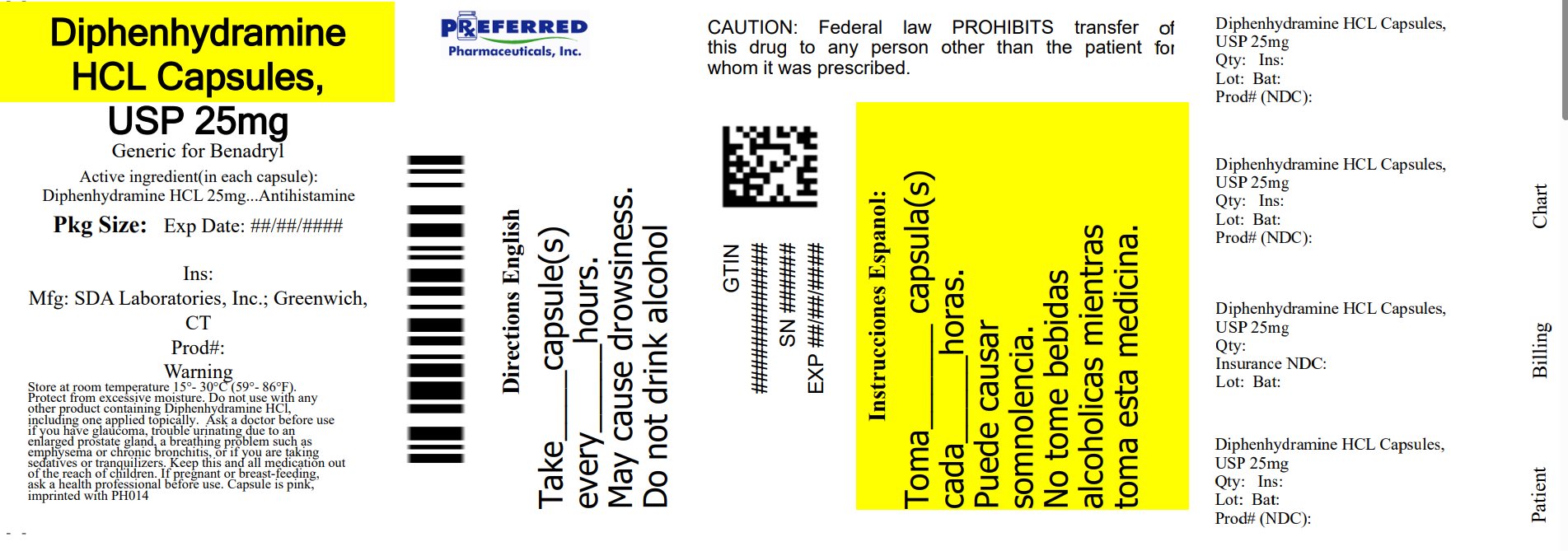 DRUG LABEL: Diphenhydramine HCL
NDC: 68788-9687 | Form: CAPSULE
Manufacturer: Preferred Pharmaceuticals, Inc.
Category: otc | Type: HUMAN OTC DRUG LABEL
Date: 20250327

ACTIVE INGREDIENTS: DIPHENHYDRAMINE HYDROCHLORIDE 25 mg/1 1
INACTIVE INGREDIENTS: FERROSOFERRIC OXIDE; D&C RED NO. 28; FD&C BLUE NO. 1; FD&C RED NO. 40; GELATIN, UNSPECIFIED; LACTOSE MONOHYDRATE; MAGNESIUM STEARATE; SILICON DIOXIDE; SODIUM LAURYL SULFATE

Drug Facts

Active Ingredient (in each capsule)

Diphenhydramine HCL 25 mg
Diphenhydramine HCL 50 mg

Purpose

Antihistamine

Uses:

- Temporarily relieves these symptoms associated with the common cold, hay fever, or other respiratory allergies.
- Sneezing.
- Nasal congestion.
- Runny nose.
- Itchy, watery eyes.

Do not use

- With any other product containing Diphenhydramine HCL, including one applied topically.

Ask a doctor or pharmacist before use

If you have

- Trouble urinating due to enlarged prostate gland
- A breathing problem such as emphysema or chronic bronchitis
- Glaucoma
- If you are taking sedatives or tranquilizers

When using this product

- Avoid alcoholic drinks.
- Marked drowsiness may occur.
- Excitability may occur, especially in children.
- Alcohol, sedatives and tranquilizers may increase drowsiness.
- Be careful when driving a motor vehicle or operating machinery.

If pregnant or breast-feeding,

ask a health professional before use.

Keep out of reach of children

In case of overdose, get medical help or contact a Poison Control Center right away.

Directions:

- Take every 4-6 hours
- Do not take more than 6 doses in 24 hours.

Adults and children 12 years or over | 1 to 2 capsule
Children 6 to under 12 years | 1 capsule
Children under 6 years | ask a doctor

Other information:

- Store at room temperature 15-30 degrees C (59-86 degrees F)
- Protect from excessive moisture

Inactive ingredients: Black Iron Oxide, D & C Red #28, FD & C Blue #1, FD & C Red #40, Gelatin, Lactose Monohydrate, Magnesium Stearate, Silicon Dioxid, Sodium Lauryl Sulfate

Relabeled By: Preferred Pharmaceuticals Inc.